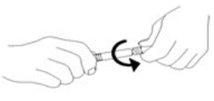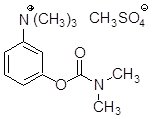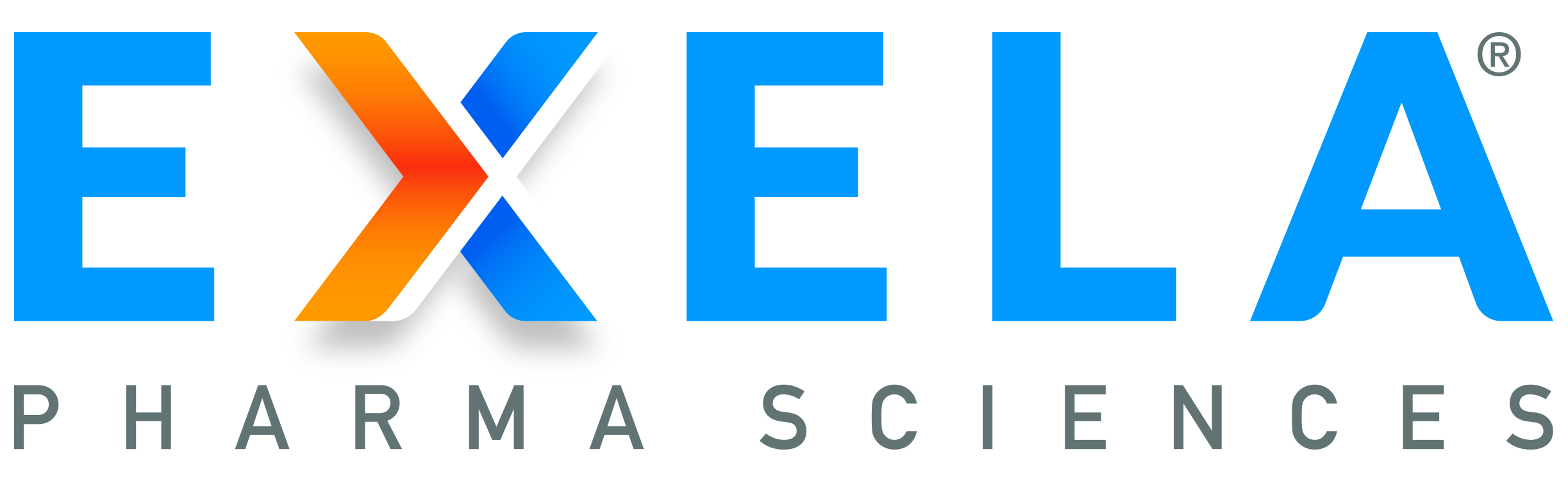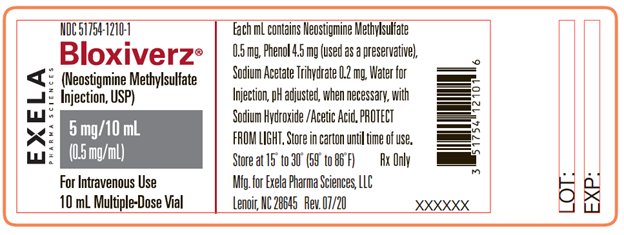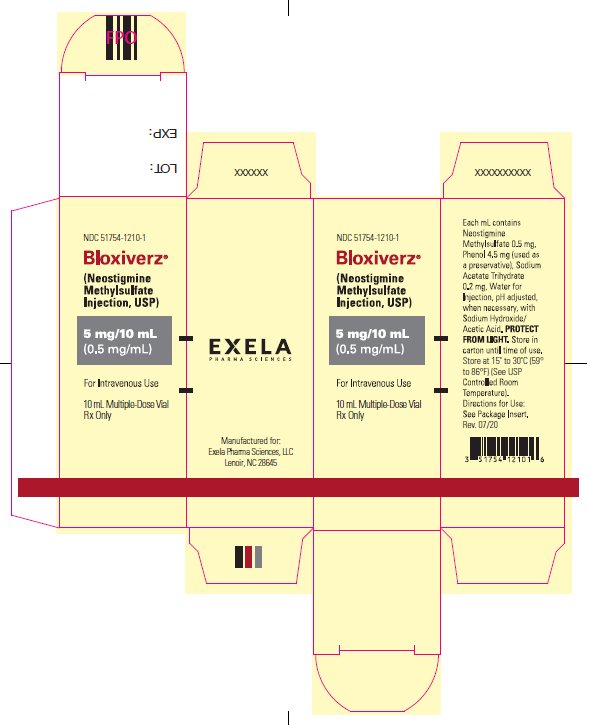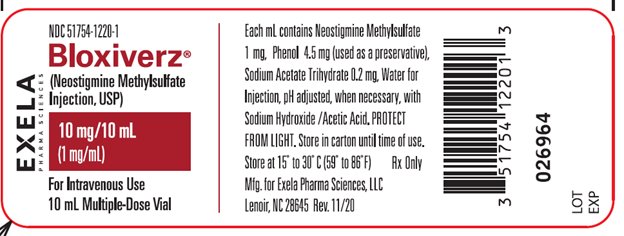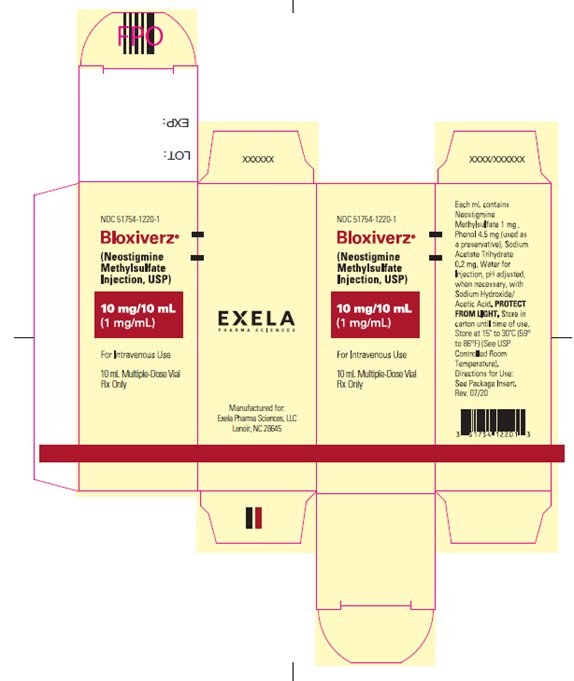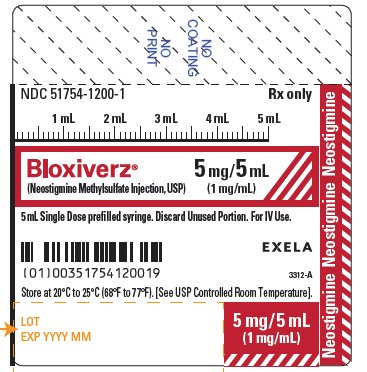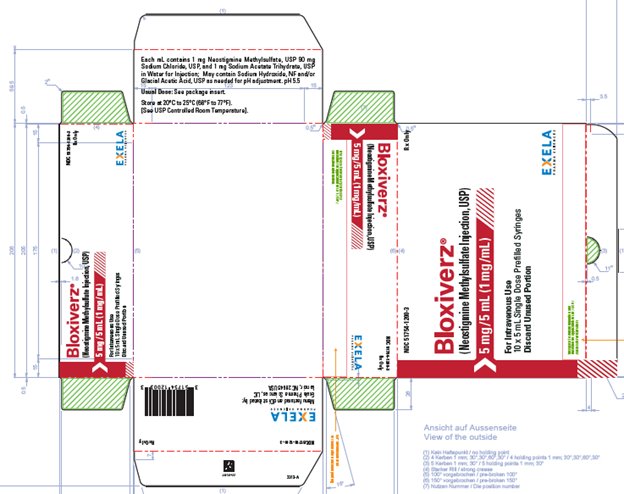 DRUG LABEL: Bloxiverz
NDC: 51754-1210 | Form: INJECTION
Manufacturer: Exela Pharma Sciences, LLC
Category: prescription | Type: HUMAN PRESCRIPTION DRUG LABEL
Date: 20231231

ACTIVE INGREDIENTS: NEOSTIGMINE METHYLSULFATE 0.5 mg/1 mL
INACTIVE INGREDIENTS: PHENOL 4.5 mg/1 mL; SODIUM ACETATE 0.2 mg/1 mL; WATER; ACETIC ACID; SODIUM HYDROXIDE

HIGHLIGHTS OF PRESCRIBING INFORMATION

These highlights do not include all the information needed to use BLOXIVERZ® safely and effectively. See full prescribing information for BLOXIVERZ.
BLOXIVERZ (Neostigmine Methylsulfate Injection), for intravenous use
Initial U.S. Approval: 1939

1 INDICATIONS AND USAGE

BLOXIVERZ, is a cholinesterase inhibitor, indicated for the reversal of the effects of non-depolarizing neuromuscular blocking agents after surgery (1).

2 DOSAGE AND ADMINISTRATION

- Should be administered by trained healthcare providers (2.1)
- Peripheral nerve stimulator and monitoring for twitch responses should be used to determine when BLOXIVERZ should be initiated and if additional doses are needed (2.2)
  - For reversal of NMBAs with shorter half-lives, when first twitch response is substantially greater than 10% of baseline, or when a second twitch is present: 0.03 mg/kg by intravenous route (2.2)
  - For reversal of NMBAs with longer half-lives or when first twitch response is close to 10% of baseline: 0.07 mg/kg by intravenous route (2.2)
- Maximum total dosage is 0.07 mg/kg or up to a total of 5 mg (whichever is less) (2.2)
- An anticholinergic agent, e.g., atropine sulfate or glycopyrrolate, should be administered prior to or concomitantly with BLOXIVERZ (2.4)

3 DOSAGE FORMS AND STRENGTHS

Injection: 0.5 mg/mL and 1 mg/mL in 10 mL multiple-dose vials and 1 mg/mL in 5 mL single-dose prefilled syringe (3)

4 CONTRAINDICATIONS

- Hypersensitivity to neostigmine (4)
- Peritonitis or mechanical obstruction of the intestinal or urinary tract (4)

5 WARNINGS AND PRECAUTIONS

- Bradycardia: Atropine or glycopyrrolate should be administered prior to BLOXIVERZ to lessen risk of bradycardia. (5.1)
- Serious Reactions with Coexisting Conditions: Use with caution in patients with, coronary artery disease, cardiac arrhythmias, recent acute coronary syndrome or myasthenia gravis. (5.2)
- Neuromuscular Dysfunction: Can occur if large doses of BLOXIVERZ are administered when neuromuscular blockade is minimal; reduce dose if recovery from neuromuscular blockade is nearly complete. (5.4)

6 ADVERSE REACTIONS

Most common adverse reactions during treatment: bradycardia, nausea and vomiting. (6)

To report SUSPECTED ADVERSE REACTIONS, contact Exela Pharma Sciences, LLC at 1-888-451-4321 or FDA at 1-800-FDA-1088 or www.fda.gov/medwatch.

FULL PRESCRIBING INFORMATION

1 INDICATIONS AND USAGE

BLOXIVERZ, is a cholinesterase inhibitor, indicated for the reversal of the effects of non-depolarizing neuromuscular blocking agents after surgery.

2 DOSAGE AND ADMINISTRATION

2.1. Important Dosage Information

BLOXIVERZ should be administered by trained healthcare providers familiar with the use, actions, characteristics, and complications of neuromuscular blocking agents (NMBA) and neuromuscular block reversal agents. Doses of BLOXIVERZ should be individualized, and a peripheral nerve stimulator should be used to determine the time of initiation of BLOXIVERZ and should be used to determine the need for additional doses.

BLOXIVERZ is for intravenous use only and should be injected slowly over a period of at least 1 minute. The BLOXIVERZ dosage is weight-based [see Dosage and Administration (2.2)].

Prior to BLOXIVERZ administration and until complete recovery of normal ventilation, the patient should be well ventilated and a patent airway maintained. Satisfactory recovery should be judged by adequacy of skeletal muscle tone and respiratory measurements in addition to the response to peripheral nerve stimulation.

An anticholinergic agent, e.g., atropine sulfate or glycopyrrolate, should be administered prior to or concomitantly with BLOXIVERZ [see Dosage and Administration (2.4)]

2.2 Dosage in Adults

a. Peripheral nerve stimulation devices capable of delivering a train-of-four (TOF) stimulus are essential to effectively using BLOXIVERZ.
b. There must be a twitch response to the first stimulus in the TOF of at least 10% of its baseline level, i.e., the response prior to NMBA administration, prior to the administration of BLOXIVERZ.
c. Prior to administration, visually inspect BLOXIVERZ for particulate matter and discoloration.
d. BLOXIVERZ should be injected slowly by intravenous route over a period of at least 1 minute.
e. A 0.03 mg/kg to 0.07 mg/kg dose of BLOXIVERZ will generally achieve a TOF twitch ratio of 90% (TOF0.9) within 10 to 20 minutes of administration. Dose selection should be based on the extent of spontaneous recovery that has occurred at the time of administration, the half-life of the NMBA being reversed, and whether there is a need to rapidly reverse the NMBA.
  1. The 0.03 mg/kg dose is recommended for:
    1. Reversal of NMBAs with shorter half-lives, e.g., rocuronium, or
    2. When the first twitch response to the TOF stimulus is substantially greater than 10% of baseline or when a second twitch is present.
  2. The 0.07 mg/kg dose is recommended for
    1. NMBAs with longer half-lives, e.g., vecuronium and pancuronium, or
    2. When the first twitch response is relatively weak, i.e., not substantially greater than 10% of baseline or
    3. There is need for more rapid recovery.
f. TOF monitoring should continue to be used to evaluate the extent of recovery of neuromuscular function and the possible need for an additional dose of BLOXIVERZ.
g. TOF monitoring alone should not be relied upon to determine the adequacy of reversal of neuromuscular blockade as related to a patient’s ability to adequately ventilate and maintain a patent airway following tracheal extubation.
h. Patients should continue to be monitored for adequacy of reversal from NMBAs for a period of time that would assure full recovery based on the patient’s medical condition and the pharmacokinetics of neostigmine and the NMBA used.
i. The recommended maximum total dose is 0.07 mg/kg or up to a total of 5 mg, whichever is less.

2.3 Dosage in Pediatric Patients, including Neonates

Adult guidelines should be followed when BLOXIVERZ is administered to pediatric patients. Pediatric patients require BLOXIVERZ doses similar to those for adult patients.

2.4 Anticholinergic (Atropine or Glycopyrrolate) Administration

An anticholinergic agent, e.g., atropine sulfate or glycopyrrolate, should be administered prior to or concomitantly with BLOXIVERZ. The anticholinergic agent should be administered intravenously using a separate syringe. In the presence of bradycardia, it is recommended that the anticholinergic agent be administered prior to BLOXIVERZ.

2.5 Instructions for Use of Prefilled Syringe

1. Perform visual inspection on the syringe by verifying:

- Absence of syringe damage
- Absence of external particles
- Absence of internal particles
- Proper drug color
- Drug name
- Drug strength
- Fill volume
- Route of administration
- Expiration date to be sure the drug has not expired

2. Do not remove the tamper evident seal. Push plunger rod slightly in to break the stopper loose while tip cap is still on

3. Remove tip cap and tamper evident seal by twisting off. (See Figure 1):

Figure 1.

4. Discard the tip cap.

5. Expel air bubble.

6. Adjust dose into sterile material (if applicable).

7. Connect the syringe to an appropriate intravenous connection.

- Before injection, ensure that the syringe is securely attached to the needle or needleless luer access device (NLAD).

8. Depress plunger rod to deliver medication. Ensure that pressure is maintained on the plunger rod during the entire administration.

9. Remove syringe from NLAD (if applicable) and discard into appropriate receptacle.

- To prevent needle stick injuries, do not recap needle when needle is connected to syringe.

NOTES:

All steps must be done sequentially
- Do not re-sterilize syringe
- Do not use this product on a sterile field
- Do not introduce any other fluid into the syringe at any time
- This product is for single dose only

3 DOSAGE FORMS AND STRENGTHS

BLOXIVERZ is available as

- Injection: 0.5 mg/mL, 5 mg of neostigmine methylsulfate in 10 mL multiple- dose vials
- Injection: 1 mg/mL, 10 mg of neostigmine methylsulfate in 10 mL multiple-dose vials
- Injection: 1 mg/mL, 5 mg of neostigmine methylsulfate in 5 mL single-dose prefilled syringe.

4 CONTRAINDICATIONS

BLOXIVERZ is contraindicated in patients with:

- known hypersensitivity to neostigmine methylsulfate (known hypersensitivity reactions have included urticaria, angioedema, erythema multiforme, generalized rash, facial swelling, peripheral edema, pyrexia, flushing, hypotension, bronchospasm, bradycardia and anaphylaxis).
- peritonitis or mechanical obstruction of the intestinal or urinary tract.

5 WARNINGS AND PRECAUTIONS

5.1 Bradycardia

Neostigmine has been associated with bradycardia. Atropine sulfate or glycopyrrolate should be administered prior to BLOXIVERZ to lessen the risk of bradycardia [see Dosage and Administration (2.4)].

5.2 Serious Adverse Reactions in Patients with Certain Coexisting Conditions

BLOXIVERZ should be used with caution in patients with coronary artery disease, cardiac arrhythmias, recent acute coronary syndrome or myasthenia gravis. Because of the known pharmacology of neostigmine methylsulfate as an acetylcholinesterase inhibitor, cardiovascular effects such as bradycardia, hypotension or dysrhythmia would be anticipated. In patients with certain cardiovascular conditions such as coronary artery disease, cardiac arrhythmias or recent acute coronary syndrome, the risk of blood pressure and heart rate complications may be increased. Risk of these complications may also be increased in patients with myasthenia gravis. Standard antagonism with anticholinergics (e.g., atropine) is generally successful to mitigate the risk of cardiovascular complications.

5.3 Hypersensitivity

Because of the possibility of hypersensitivity, atropine and medications to treat anaphylaxis should be readily available.

5.4 Neuromuscular Dysfunction

Large doses of BLOXIVERZ administered when neuromuscular blockade is minimal can produce neuromuscular dysfunction. The dose of BLOXIVERZ should be reduced if recovery from neuromuscular blockade is nearly complete.

5.5 Cholinergic Crisis

It is important to differentiate between myasthenic crisis and cholinergic crisis caused by overdosage of BLOXIVERZ. Both conditions result in extreme muscle weakness but require radically different treatment [see Overdosage (10)].

6 ADVERSE REACTIONS

6.1 Clinical Trials Experience

Because clinical trials are conducted under widely varying conditions, adverse reaction rates observed in the clinical trials of a drug cannot be directly compared to rates in the clinical trials of another drug and may not reflect the rates observed in practice.

Adverse reactions to neostigmine methylsulfate are most often attributable to exaggerated pharmacological effects, in particular, at muscarinic receptor sites. The use of an anticholinergic agent, e.g., atropine sulfate or glycopyrrolate, may prevent or mitigate these reactions.

Quantitative adverse event data are available from trials of neostigmine methylsulfate in which 200 adult patients were exposed to the product. The following table lists the adverse reactions that occurred with an overall frequency of 1% or greater.

System Organ Class | Adverse Reaction
Cardiovascular Disorders | bradycardia, hypotension, tachycardia/heart rate increase
Gastrointestinal Disorders | dry mouth, nausea, post-procedural nausea, vomiting
General Disorders and Administration Site Conditions | incision site complication, pharyngolaryngeal pain, procedural complication, procedural pain
Nervous System Disorders | dizziness, headache, postoperative shivering, prolonged neuromuscular blockade
Psychiatric Disorders | insomnia
Respiratory, Thoracic and Mediastinal Disorders | dyspnea, oxygen desaturation <90%
Skin and Subcutaneous Tissue Disorders | pruritus

6.2 Post Marketing Experience

The following adverse reactions have been identified during parenteral use of neostigmine methylsulfate. Because these reactions are reported voluntarily from a population of uncertain size, it is not always possible to reliably estimate their frequency or establish a causal relationship to drug exposure.

System Organ Class | Adverse Reaction
Allergic Disorders | allergic reactions, anaphylaxis
Nervous System Disorders | convulsions, drowsiness, dysarthria, fasciculation, loss of consciousness, miosis, visual changes
Cardiovascular Disorders | cardiac arrest, cardiac arrhythmias (A-V block, nodal rhythm), hypotension, nonspecific EKG changes, syncope
Respiratory, Thoracic and Mediastinal Disorders | bronchospasm; increased oral, pharyngeal and bronchial secretions; respiratory arrest; respiratory depression
Skin and Sub-cutaneous Tissue Disorders | rash, urticaria
Gastrointestinal Disorders | bowel cramps, diarrhea, flatulence, increased peristalsis
Renal and Urinary Disorders | urinary frequency
Musculoskeletal and Connective Tissue Disorders | arthralgia, muscle cramps, spasms, weakness
Miscellaneous | diaphoresis, flushing

7 DRUG INTERACTIONS

The pharmacokinetic interaction between neostigmine methylsulfate and other drugs has not been studied. Neostigmine methylsulfate is metabolized by microsomal enzymes in the liver. Use with caution when using BLOXIVERZ with other drugs which may alter the activity of metabolizing enzymes or transporters.

8 USE IN SPECIFIC POPULATIONS

8.1 Pregnancy

Risk Summary

Published studies and case reports over several decades about the use of neostigmine products, including neostigmine methylsulfate, in pregnant women have not identified any drug-associated risk for major birth defects and miscarriage. However, most of the available data are based on studies with exposure that occurred at the time of caesarean section or labor and delivery. These studies have not identified an adverse effect on maternal or infant outcomes. In animal reproduction studies, no adverse developmental effects were observed after administration of neostigmine methylsulfate to pregnant rats and rabbits during organogenesis with doses up to 0.1 and 0.2 times, respectively, the maximum recommended human dose (MRHD) of 5mg/60kg/person/day based on body surface area (mg/m^2).

The background risk of major birth defects and miscarriage for the indicated population is unknown. All pregnancies have a background risk of birth defect, loss, or other adverse outcomes. In the U.S. general population, the estimated background risk of major birth defects and miscarriage in the clinically recognized pregnancies is 2 to 4% and 15 to 20% respectively.

Data

Animal Data

In embryofetal development studies, rats and rabbits were administered neostigmine methylsulfate at human equivalent doses (HED, on a mg/m^2 basis) of 1.6, 4 and 8.1 mcg/kg/day and 3.2, 8.1, and 13 mcg/kg/day, respectively, during the period of organogenesis (Gestation Days 6 through 17 for rats and Gestation Days 6 through 18 for rabbits). There was no evidence for a teratogenic effect in rats and rabbits up to HED 8.1 and 13 mcg/kg/day, which are approximately 0.097 times and 0.16 times the MRHD of 5 mg/60 kg, respectively in the presence of minimal maternal toxicity (tremors, ataxia, and prostration). The studies resulted in exposures in the animals well below predicted exposures in humans.

In a pre- and postnatal development study in rats, neostigmine methylsulfate was administered to pregnant female rats at human equivalent doses (HED) of 1.6, 4 and 8.1 mcg/kg/day from Day 6 of gestation through Day 20 of lactation, with weaning on Day 21. There were no adverse effects on physical development, behavior, learning ability, or fertility in the offspring at HED doses up to 8.1 mcg/kg/day which is 0.097 times the MRHD of 5 mg/60 kg on a mg/m^2 basis in the presence of minimal maternal toxicity (tremors, ataxia, and prostration). The studies resulted in exposures in the animals well below predicted exposures in humans.

8.2 Lactation

Risk Summary

Published data from case reports are insufficient to determine the presence of neostigmine methylsulfate in human milk or the effects on the breastfed infant. There is no information on the effects of neostigmine on milk production. The developmental and health benefits of breastfeeding should be considered along with the mother’s clinical need for BLOXIVERZ and any potential adverse effects on the breastfed infant from BLOXIVERZ or from the underlying maternal condition.

8.4 Pediatric Use

BLOXIVERZ is approved for the reversal of the effects of non-depolarizing neuromuscular blocking agents after surgery in pediatric patients of all ages.

Recovery of neuromuscular activity occurs more rapidly with smaller doses of cholinesterase inhibitors in infants and children than in adults. However, infants and small children may be at greater risk of complications from incomplete reversal of neuromuscular blockade due to decreased respiratory reserve. The risks associated with incomplete reversal outweigh any risk from giving higher doses of BLOXIVERZ (up to 0.07 mg/kg or up to a total of 5 mg, whichever is less).

The dose of BLOXIVERZ required to reverse neuromuscular blockade in children varies between 0.03 mg - 0.07 mg/kg, the same dose range shown to be effective in adults, and should be selected using the same criteria as used for adult patients [see Clinical Pharmacology (12.3)].

Since the blood pressure in pediatric patients, particularly infants and neonates, is sensitive to changes in heart rate, the effects of an anticholinergic agent (e.g., atropine) should be observed prior to administration of neostigmine to lessen the probability of bradycardia and hypotension.

8.5 Geriatric Use

Because elderly patients are more likely to have decreased renal function, BLOXIVERZ should be used with caution and monitored for a longer period in elderly patients. The duration of action of neostigmine methylsulfate is prolonged in the elderly; however, elderly patients also experience slower spontaneous recovery from neuromuscular blocking agents. Therefore, dosage adjustments are not generally needed in geriatric patients; however, they should be monitored for longer periods than younger adults to assure additional doses of BLOXIVERZ are not required. The duration of monitoring should be predicated on the anticipated duration of action for the NMBA used on the patient [see Dosage and Administration (2.3)].

8.6. Renal Impairment

Elimination half-life of neostigmine methylsulfate was prolonged in anephric patients compared to normal subjects.

Although no adjustments to BLOXIVERZ dosing appear to be warranted in patients with impaired renal function, they should be closely monitored to assure the effects of the neuromuscular blocking agent, particularly one cleared by the kidneys, do not persist beyond those of BLOXIVERZ. In this regard, the interval for re-dosing the neuromuscular blocking agent during the surgical procedure may be useful in determining whether, and to what extent, post-operative monitoring needs to be extended.

8.7. Hepatic Impairment

The pharmacokinetics of neostigmine methylsulfate in patients with hepatic impairment have not been studied. Neostigmine methylsulfate is metabolized by microsomal enzymes in the liver. No adjustments to the dosing of BLOXIVERZ appear to be warranted in patients with hepatic insufficiency. However, patients should be carefully monitored if hepatically cleared neuromuscular blocking agents were used during their surgical procedure as their duration of action may be prolonged by hepatic insufficiency whereas BLOXIVERZ, which undergoes renal elimination, will not likely be affected. This could result in the effects of the neuromuscular blocking agent outlasting those of BLOXIVERZ. This same situation may arise if the neuromuscular blocking agent has active metabolites. In this regard, the interval for re-dosing the neuromuscular blocking agent during the surgical procedure may be useful in determining whether, and to what extent, post-operative monitoring needs to be extended.

10 OVERDOSAGE

Muscarinic symptoms (nausea, vomiting, diarrhea, sweating, increased bronchial and salivary secretions, and bradycardia) may appear with overdosage of BLOXIVERZ (cholinergic crisis), but may be managed by the use of additional atropine or glycopyrrolate. The possibility of iatrogenic overdose can be lessened by carefully monitoring the muscle twitch response to peripheral nerve stimulation. Should overdosage occur, ventilation should be supported by artificial means until the adequacy of spontaneous respiration is assured, and cardiac function should be monitored.

Overdosage of BLOXIVERZ can cause cholinergic crisis, which is characterized by increasing muscle weakness, and through involvement of the muscles of respiration, may result in death. Myasthenic crisis, due to an increase in the severity of the disease, is also accompanied by extreme muscle weakness and may be difficult to distinguish from cholinergic crisis on a symptomatic basis. However, such differentiation is extremely important because increases in the dose of BLOXIVERZ or other drugs in this class, in the presence of cholinergic crisis or of a refractory or “insensitive” state, could have grave consequences. The two types of crises may be differentiated by the use of edrophonium chloride as well as by clinical judgment.

Treatment of the two conditions differs radically. Whereas the presence of myasthenic crisis requires more intensive anticholinesterase therapy, cholinergic crisis calls for the prompt withdrawal of all drugs of this type. The immediate use of atropine in cholinergic crisis is also recommended. Atropine may also be used to lessen gastrointestinal side effects or other muscarinic reactions; but such use, by masking signs of overdosage, can lead to inadvertent induction of cholinergic crisis.

11 DESCRIPTION

Neostigmine methylsulfate, a cholinesterase inhibitor, is (m-hydroxyphenyl) trimethylammonium methylsulfate dimethylcarbamate. The structural formula is:

Neostigmine methylsulfate is a white crystalline powder and is very soluble in water and soluble in alcohol. BLOXIVERZ is a sterile, nonpyrogenic solution intended for intravenous use.

Each mL of the 0.5 mg/mL strength contains neostigmine methylsulfate 0.5 mg, phenol 4.5 mg (used as preservative) and sodium acetate trihydrate 0.2 mg, in water for injection. The pH is adjusted, when necessary, with acetic acid/sodium hydroxide to achieve a value of 5.5.

Each mL of the 1 mg/mL strength contains neostigmine methylsulfate 1 mg, phenol 4.5 mg (used as preservative), and sodium acetate trihydrate 0.2 mg, in water for injection. The pH is adjusted, when necessary, with acetic acid/sodium hydroxide to achieve a value of 5.5.

Each mL of the 5 mL single-dose prefilled syringe contains 1 mg neostigmine methylsulfate, USP, 90 mg sodium chloride, USP and 1 mg sodium acetate trihydrate, USP in water for injection. May contain sodium hydroxide, NF and/or glacial acetic acid, USP as needed for pH adjustment to achieve a value of 5.5.

12 CLINICAL PHARMACOLOGY

12.1 Mechanism of Action

Neostigmine methylsulfate is a competitive cholinesterase inhibitor. By reducing the breakdown of acetylcholine, neostigmine methylsulfate induces an increase in acetylcholine in the synaptic cleft which competes for the same binding site as nondepolarizing neuromuscular blocking agents, and reverses the neuromuscular blockade.

12.2 Pharmacodynamics

Neostigmine methylsulfate-induced increases in acetylcholine levels results in the potentiation of both muscarinic and nicotinic cholinergic activity. The resulting elevation of acetylcholine competes with nondepolarizing neuromuscular blocking agents to reverse neuromuscular blockade. Neostigmine methylsulfate does not readily cross the blood-brain barrier and, therefore, does not significantly affect cholinergic function in the central nervous system.

12.3 Pharmacokinetics

Distribution: Following intravenous injection, the observed neostigmine methylsulfate volume of distribution is reported between 0.12 and 1.4 L/kg. Protein binding of neostigmine methylsulfate to human serum albumin ranges from 15 to 25%.

Metabolism: Neostigmine methylsulfate is metabolized by microsomal enzymes in the liver.

Elimination: Following intravenous injection, the reported elimination half-life of neostigmine methylsulfate is between 24 and 113 minutes. Total body clearance of neostigmine methylsulfate is reported between 1.14 and 16.7 mL/min/kg.

Renal impairment: Elimination half-life of neostigmine methylsulfate was prolonged in anephric patients compared to normal subjects; elimination half-life for normal, transplant and anephric patients were 79.8 ± 48.6, 104.7 ± 64 and 181 ± 54 min (mean ± SD), respectively.

Hepatic impairment: The pharmacokinetics of neostigmine methylsulfate in patients with hepatic impairment has not been studied.

Pediatrics: Elimination half-life of neostigmine methylsulfate in infants (2-10 months), children (1-6 years) and adults (29-48 years) were 39 ± 5 min, 48 ± 16 min, and 67 ± 8 min (mean ± SD), respectively. Observed neostigmine methylsulfate clearance for infants, children and adults were 14 ± 3, 11 ± 3 and 10 ± 2 mL/min/kg (mean ± SD), respectively.

Drug Interaction Studies: The pharmacokinetic interaction between neostigmine methylsulfate and other drugs has not been studied.

13 NONCLINICAL TOXICOLOGY

13.1 Carcinogenesis, Mutagenesis, Impairment of Fertility

Carcinogenesis: Long-term animal studies have not been performed to evaluate the carcinogenic potential of neostigmine.

Genotoxicity: Neostigmine methylsulfate was not mutagenic or clastogenic when evaluated in an in vitro bacterial reverse mutation assay (Ames test), an in vitro Chinese hamster ovary cell chromosomal aberration assay, or an in vivo mouse bone marrow micronucleus assay.

Impairment of Fertility: In a fertility and early embryonic development study in rats, male rats were treated for 28 days prior to mating and female rats were treated for 14 days prior to mating with intravenous neostigmine methylsulfate (human equivalent doses of 1.6, 4, and 8.1 mcg/kg/day, based on body surface area). No adverse effects were reported at any dose (up to 0.1 times the MRHD of 5 mg/60 kg person based on a body surface area comparison).

14 CLINICAL STUDIES

The evidence for the efficacy of neostigmine methylsulfate for the reversal of the effects of non-depolarizing neuromuscular blocking agents after surgery is derived from the published literature. Randomized, spontaneous-recovery or placebo-controlled studies using similar efficacy endpoints evaluated a total of 404 adult and 80 pediatric patients undergoing various surgical procedures. Patients had reductions in their recovery time from neuromuscular blockade with neostigmine methylsulfate treatment compared to spontaneous recovery.

16 HOW SUPPLIED/STORAGE AND HANDLING

BLOXIVERZ (Neostigmine Methylsulfate Injection, USP) is available in the following:

NDC No. | Strength | Vial Size
51754-1210-3 | 0.5 mg/mL | 10 mL multiple-dose vials (supplied in packages of 10)
51754-1220-3 | 1 mg/mL | 10 mL multiple-dose vials (supplied in packages of 10)
51754-1200-3 | 1 mg/mL | 5 mL single-dose prefilled syringe (supplied in packages of 10)

The vial stopper is not made with natural rubber latex.

STORAGE AND HANDLING

BLOXIVERZ should be stored at 20° to 25°C (68° to 77°F); excursions permitted to 15° to 30°C (59° to 86°F) (see USP Controlled Room Temperature). Protect from light. Store in carton until time of use.

Manufactured for:

Exela Pharma Sciences, LLC

Lenoir, NC 28645

PACKAGE/LABEL PRINCIPAL DISPLAY PANEL- 0.5 mg/mL Vial Label

NDC 51754-1210-1

Bloxiverz

(Neostigmine Methylsulfate

Injection, USP)

5 mg/10 mL

(0.5 mg/mL)

For Intravenous Use

10 mL Multiple-Dose Vial

PACKAGE/LABEL PRINCIPAL DISPLAY PANEL-0.5 mg/mL Carton Label

NDC 51754-1210-1

Bloxiverz

(Neostigmine

Methylsulfate

Injection, USP)

5 mg/10 mL

(0.5 mg/mL)

For Intravenous Use

10 mL Multiple-Dose Vial

Rx Only

PACKAGE/LABEL PRINCIPAL DISPLAY PANEL- 1 mg/mL Vial Label

NDC 51754-1220-1

Bloxiverz

(Neostigmine Methylsulfate

Injection, USP)

10 mg/10 mL

(1 mg/mL)

For Intravenous Use

10 mL Multiple-Dose Vial

PACKAGE/LABEL PRINCIPAL DISPLAY PANEL-1 mg Carton Label

NDC 51754-1220-1

Bloxiverz

(Neostigmine

Methylsulfate

Injection, USP)

10 mg/10 mL

(1 mg/mL)

For Intravenous Use

10 mL Multiple-Dose Vial

Rx Only

PACKAGE/LABEL PRINCIPAL DISPLAY PANEL-5 mL Syringe Label

NDC 51754-1200-1 Rx only

Bloxiverz

(Neostigmine Methylsulfate Injection, USP)

5 mg/5 mL

(1 mg/mL)

5 mL Single Dose prefilled syringe. Discard Unused Portion. For IV Use.

Store at 20°C to 25°C (68°F to 77°F). [See USP Controlled Room Temperature].

PACKAGE/LABEL PRINCIPAL DISPLAY PANEL-5 mL Syringe Carton Label

NDC 51754-1200-3 Rx only

Bloxiverz

(Neostigmine Methylsulfate Injection, USP)

5 mg/5 mL (1 mg/mL)

For Intravenous Use

10 x 5 mL Single Dose Prefilled Syringes

Discard Unused Portion